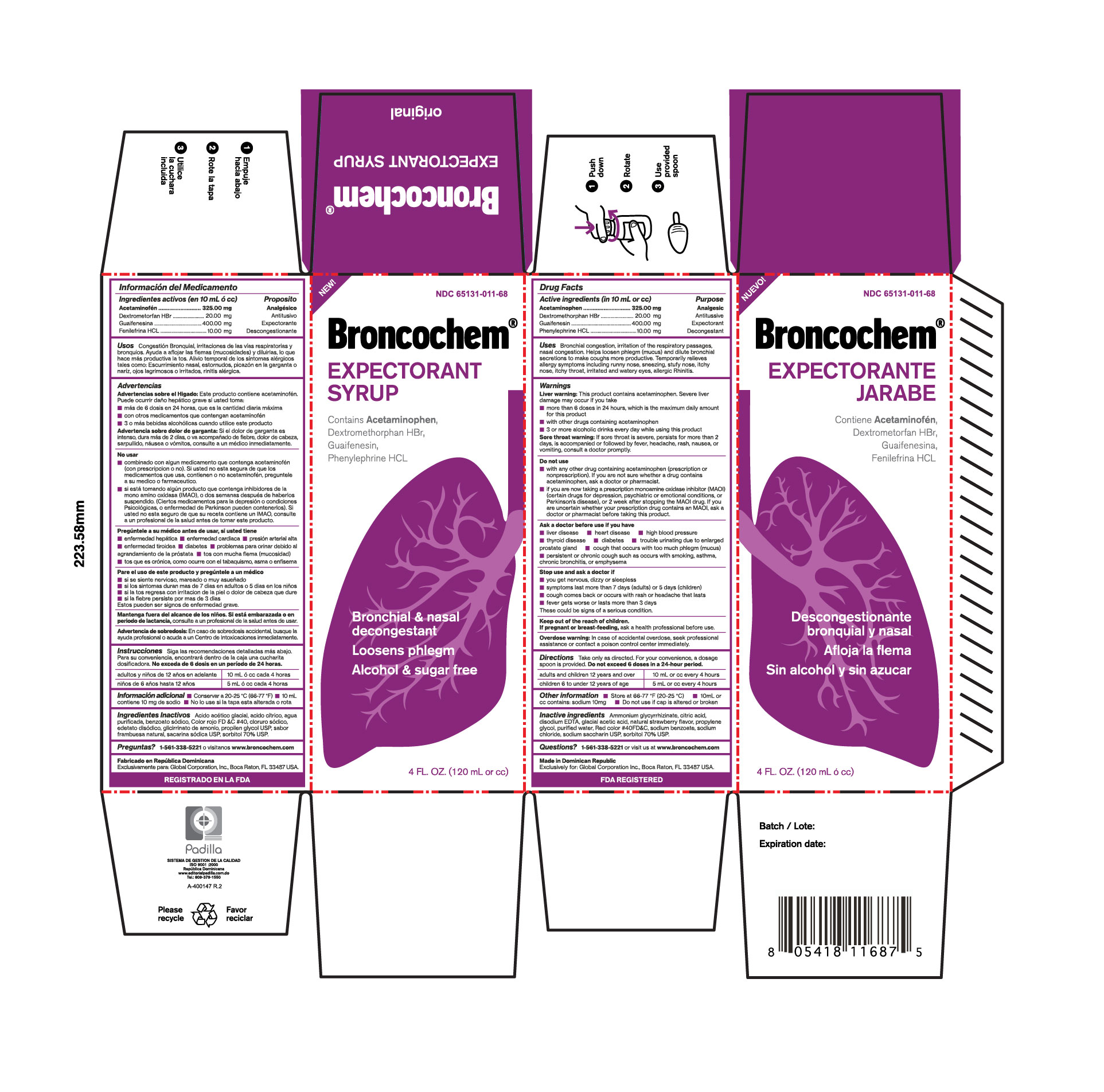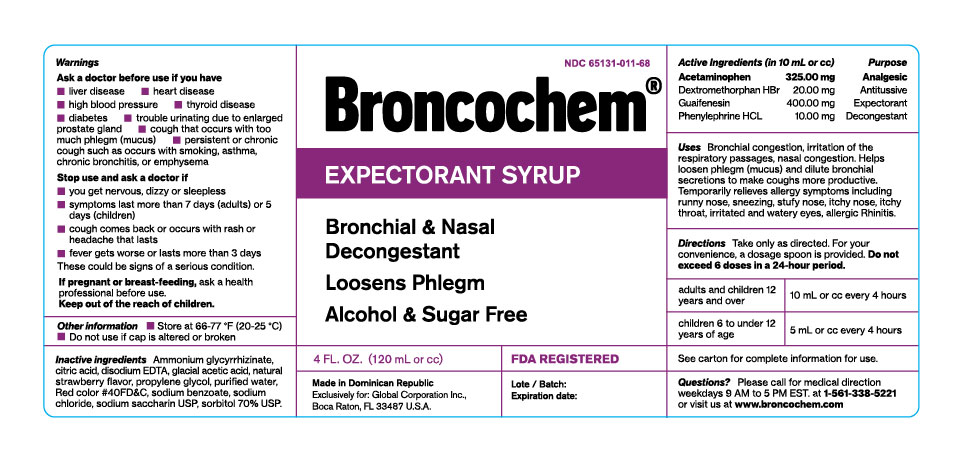 DRUG LABEL: BRONCOCHEM
NDC: 65131-011 | Form: SYRUP
Manufacturer: LABORATORIO MAGNACHEM INTERNATIONAL SRL
Category: otc | Type: HUMAN OTC DRUG LABEL
Date: 20250323

ACTIVE INGREDIENTS: ACETAMINOPHEN 325 mg/10 mL; DEXTROMETHORPHAN HYDROBROMIDE 20 mg/10 mL; GUAIFENESIN 400 mg/10 mL; PHENYLEPHRINE HYDROCHLORIDE 10 mg/10 mL
INACTIVE INGREDIENTS: SACCHARIN SODIUM 40 mg/10 mL; SODIUM BENZOATE 20 mg/10 mL; SODIUM CHLORIDE 12 mg/10 mL; AMMONIUM GLYCYRRHIZATE 6 mg/10 mL; DISODIUM HEDTA 5 mg/10 mL; CITRIC ACID MONOHYDRATE 2 mg/10 mL; SORBITOL 2.3 mL/10 mL; PROPYLENE GLYCOL 2 mL/10 mL; ACETIC ACID 0.016 mL/10 mL; RASPBERRY 0.006 mL/10 mL; FD&C RED NO. 40 0.29 mg/10 mL; WATER 10 mL/10 mL

BRONCOCHEM EXPECTORANT II

Warnings

Unless directed by a physician do not take this product if persistent or chronic cough such as occurs with smoking, asthma, chronic bronchitis, emphysema, or if cough is accompanied by excessive phlem (mucus). Likewise if you have heart disease, high blood pressure, thyroid disease, diabetes, or difficulty in urination due to enlargement of the prostate gland, if nervousness, dizziness, or sleeplesness occur, discontinue use or consult a doctor, if symptoms do not improve within 7 days or are accompainied by fever, consult a doctor. A persistent cough may be a sing of a serious condition. Stop use and ask a doctor if symptoms persist or last long that 5 days (children) or 7 days (adults), tend to return, arash, or persistent headache. As with any drug, if you are pregnant or nursing a baby; seek the advice of a healh professional before using this product. Unless directed by a doctor, do not take this product if you are presently taking another product containing Pseudoephedrine HCl, or if you are taking sedatives or trankilizers; it may increase the drowsiness effect. Avoid alcoholic beverages while taking this product. Use caution when driving a motor vehicle or operating machinery.

Active Ingredients

Acetaminophen

Dextromethorphan HBr

Guaifenesin

Phenylephrine HCl

Purpose

Analgesic

Antihistaminic

Antotussive

Expectorant

Decongestant

Keep Out Of the Reach Of children

In case of accidental overdose, seek professional assistancve or contact a poison control center inmediately

Indications & Use

Bronchial congestion

Irritation of the respiratory passages

Nasal congestion

Helps loosen phlegm (mucus) and dilute bronchial secretions to make coughs more productive

Antitussive

Temporarilly relieves allergy symptoms including runny nose, sneezing, stuffy nose, itchy nose, itchy throat, irritated and watery eyes, allergic rhinitis

Dosage and Administration

Do not exceed 6 doses in a 24 hour period

Adults and chuildren 12 years and over: (10mL or cc) using metered dosage spoon every 4 hours.

Children 6 years up to 12 years: (5mL or cc) using metered dosage spoon every 4 hours

Drug Interaction Precautions

Do not use if you are now taking a prescription monoamine oxidase inhibitor (MAOI). (certain drugs for depression, psychiatric or emotional conditions, or Parkinson`s disease), or 2 weeks after stopping the MAOI drug. If you are uncertain whether your presciption drug contains an MAOI, consult a health professional before taking this product

Iactive Ingredient

Aloe Vera, Ammonium Glycyrrhizinate, Citric acid, Disodium EDTA, Glacial Acetic Acid, Natural Raspberry flavor, Propylene Glycol USP, Purified Water, FD&C Red No.40, Sodium Benzoate, Sodium Saccharin USP, Sorbitol 70%.